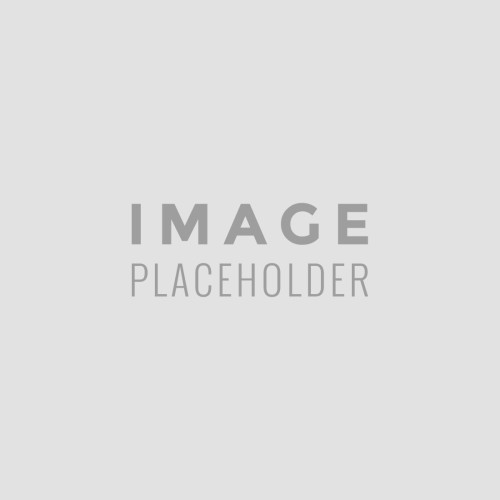 DRUG LABEL: Quality Choice Maximum Strength Triple Antibiotic
NDC: 63868-009 | Form: OINTMENT
Manufacturer: Chain Drug Marketing Association Inc
Category: otc | Type: HUMAN OTC DRUG LABEL
Date: 20191219

ACTIVE INGREDIENTS: NEOMYCIN SULFATE 3.5 mg/1 g; BACITRACIN ZINC 500 [USP'U]/1 g; PRAMOXINE HYDROCHLORIDE 10 mg/1 g; POLYMYXIN B SULFATE 10000 [USP'U]/1 g
INACTIVE INGREDIENTS: LIGHT MINERAL OIL; POLYOXYL 40 STEARATE; PETROLATUM; STEARIC ACID; CETYL ALCOHOL

QC Max Strength Triple Antibiotic Ointment 1 oz. 94594 CMI 2019

Active ingredient (in each gram) Purposes

Bacitracin zinc 500 units.........................................................First aid antibiotic

Neomycin sulfate 3.5 mg........................................................First aid antibiotic

Polymyxin B sulfate 10,000 units............................................First aid antibiotic

Pramoxine HCI 10 mg.............................................................External analgesic

Uses

- first aid to help prevent infection and for the temporary relief of pain in minor:
- cuts
- scrapes
- burns

Warnings

For external use only

Do not use

- if you are allergic to any of the ingredients
- in the eyes or nose
- over large areas of the body

Ask a doctor before use if you have

- deep or puncture wounds
- animal bites
- serious burns

Stop use and ask a doctor if

- you need to use longer than 1 week
- rash or other allergic reaction develops
- symptoms persist for more than 1 week, or clear up and occur again within a few days
- condition persists or gets worse
- redness, irritation, swelling, or pain persists or increases

PREGNANCY OR BREAST FEEDING

If pregnant or breast-feeding, ask a health professional before use

Keep out of reach of children. If swallowed, get medical help or contact a Poison Control Center (1-800-222-1222) right away.

Directions

- adults and children 2 years of age and older:
- clean the affected area
- apply a small amount of this product (an amount equal to the surface area of the tip of a finger) on the area 1 to 3 times daily
- may be covered with a sterile bandage
- children under 2 years of age: ask a doctor

Other information

- store at room temperature 20-25°C (68-77°F)

Inactive ingredients

cetyl alcohol, light mineral oil, polyoxyl 40 stearate, stearic acid, white petrolatum

DOSAGE AND ADMINISTRATION

Distributed by:

C.D.M.A., Inc.

43157 W 9 Mile Rd

Novi, MI 48375

www.qualitychoice.com

Made in South Korea